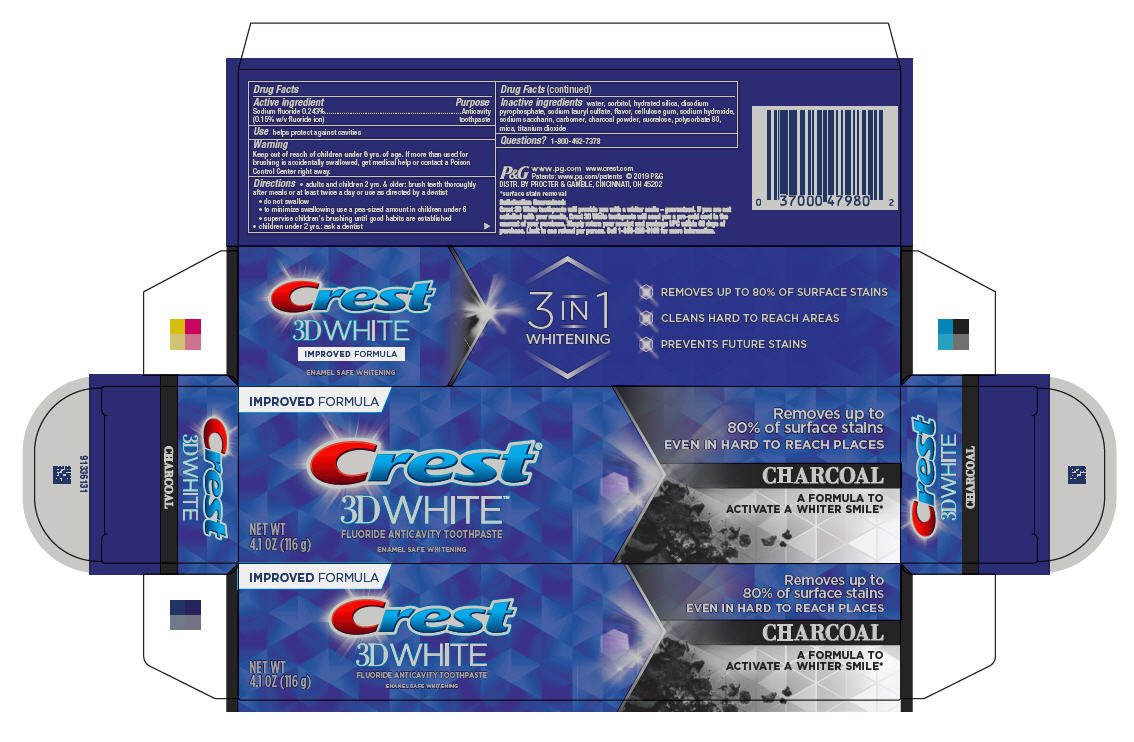 DRUG LABEL: Crest 3D White
NDC: 37000-945 | Form: PASTE, DENTIFRICE
Manufacturer: Procter & Gamble Manfuacturing Company
Category: otc | Type: HUMAN OTC DRUG LABEL
Date: 20260108

ACTIVE INGREDIENTS: SODIUM FLUORIDE 1.5 mg/1 g
INACTIVE INGREDIENTS: CARBOXYPOLYMETHYLENE; SODIUM ACID PYROPHOSPHATE; CARBOXYMETHYLCELLULOSE SODIUM; ACTIVATED CHARCOAL; POLYSORBATE 80; WATER; SACCHARIN SODIUM; HYDRATED SILICA; SODIUM LAURYL SULFATE; SUCRALOSE; TITANIUM DIOXIDE; SORBITOL; SODIUM HYDROXIDE; MICA

Crest®
3D White™
Charcoal

Drug Facts

Active ingredient

Sodium fluoride 0.243% (0.15% w/v fluoride ion)

Purpose

Anticavity toothpaste

Use

helps protect against cavities

Warnings

Keep out of reach of children under 6 yrs. of age. If more than used for brushing is accidentally swallowed, get medical help or contact a Poison Control Center right away.

Directions

- adults and children 2 yrs. & older: brush teeth thoroughly after meals or at least twice a day or use as directed by a dentist
  - do not swallow
  - to minimize swallowing use a pea-sized amount in children under 6
  - supervise children's brushing until good habits are established
- children under 2 yrs.: ask a dentist

Inactive ingredients

water, sorbitol, hydrated silica, disodium pyrophosphate, sodium lauryl sulfate, flavor, cellulose gum, sodium hydroxide, sodium saccharin, carbomer, charcoal powder, sucralose, polysorbate 80, mica, titanium dioxide

Questions?

1-800-492-7378

DISTR. BY PROCTER & GAMBLE,

CINCINNATI, OH 45202

PRINCIPAL DISPLAY PANEL - 116 g Carton

IMPROVED FORMULA

Crest®

3D WHITE™

FLUORIDE ANTICAVITY TOOTHPASTE

NET WT 4.1 OZ (116 g)

ENAMEL SAFE WHITENING

Removes up to
80% of surface stains
EVEN IN HARD TO REACH PLACES

CHARCOAL

A FORMULA TO ACTIVATE A WHITER SMILE*